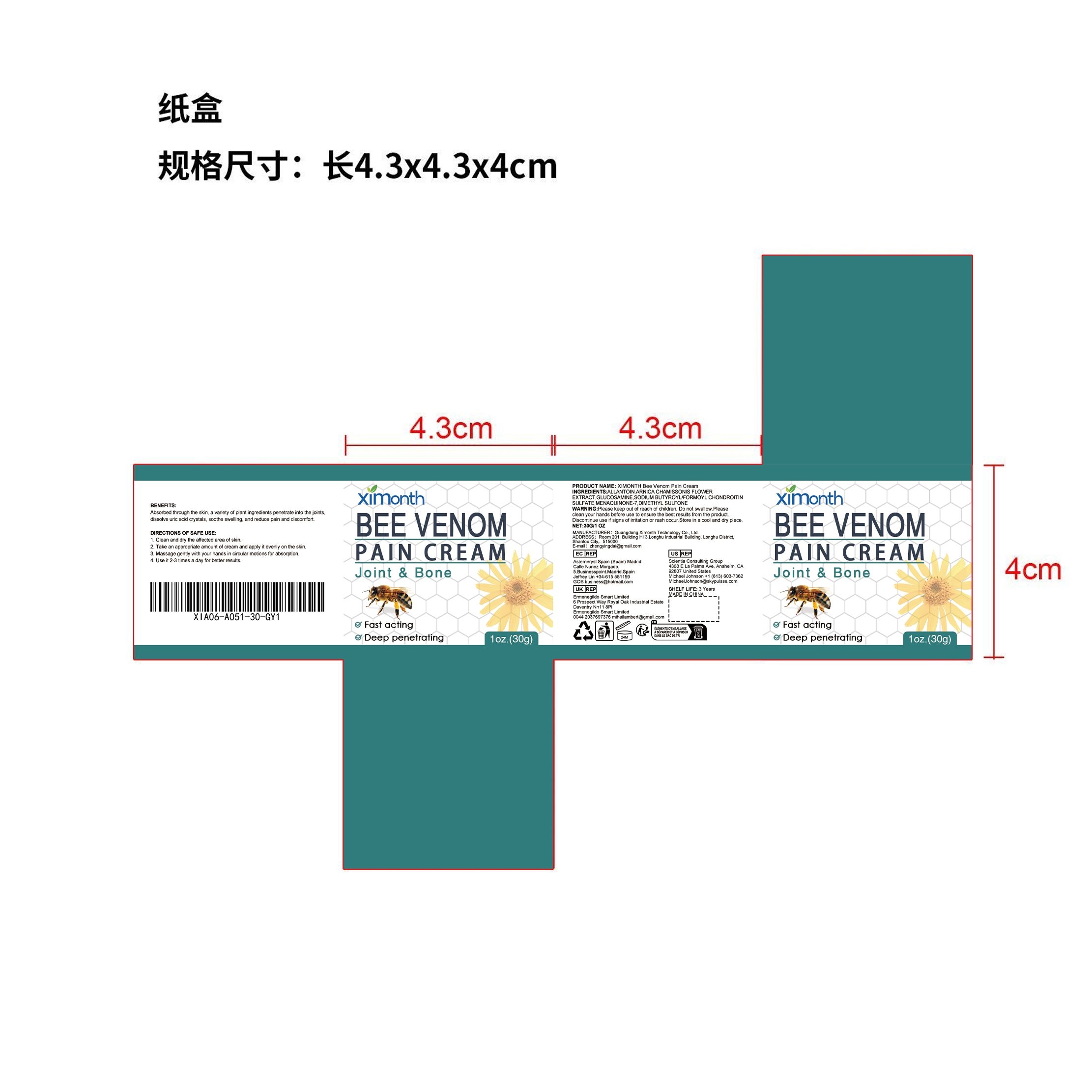 DRUG LABEL: XIMONTH Bee Venom Pain Cream
NDC: 84660-033 | Form: CREAM
Manufacturer: Guangdong Ximonth Technology Co., Ltd.
Category: otc | Type: HUMAN OTC DRUG LABEL
Date: 20240926

ACTIVE INGREDIENTS: GLUCOSAMINE 4.5 g/30 g; MENAQUINONE 7 9 g/30 g; ARNICA CHAMISSONIS FLOWER 3 g/30 g; DIMETHYL SULFONE 3 g/30 g
INACTIVE INGREDIENTS: ALLANTOIN 6 g/30 g; SODIUM BUTYROYL/FORMOYL HYALURONATE 4.5 g/30 g

Active Ingredient(s)

ARNICA CHAMISSONIS FLOWER EXTRACT、GLUCOSAMINE、SODIUM BUTYROYL/FORMOYL CHONDROITIN SULFATE、
MENAQUINONE-7、DIMETHYL SULFONE

Purpose

Absorbed through the skin, a variety of plant ingredients penetrate into the joints, dissolve uric acid crystals, soothe swelling, and reduce pain and discomfort.

Use

1. Clean and dry the affected area of skin.
2. Take an appropriate amount of cream and apply it evenly on the skin.
3. Massage gently with your hands in circular motions for absorption.
4. Use it 2-3 times a day for better results.

Warnings

Please keep out of reach of children.Do not swallow.Please clean your hands before use to ensure the best results from the product.Discontinue use if signs of irritation or rash occur.Store in a cool and dry place.

Do not use

Discontinue use if signs of irritation or rash occur.

STOP USE

Discontinue use if signs of irritation or rash occur.

KEEP OUT OF REACH OF CHILDREN

Please keep out of reach of children. Do not swallow.

STORAGE AND HANDLING

Avoid freezing and excessive heat above 40C (104F) ）
Store in a cool and dry place.

INACTIVE INGREDIENT

ALLANTOIN